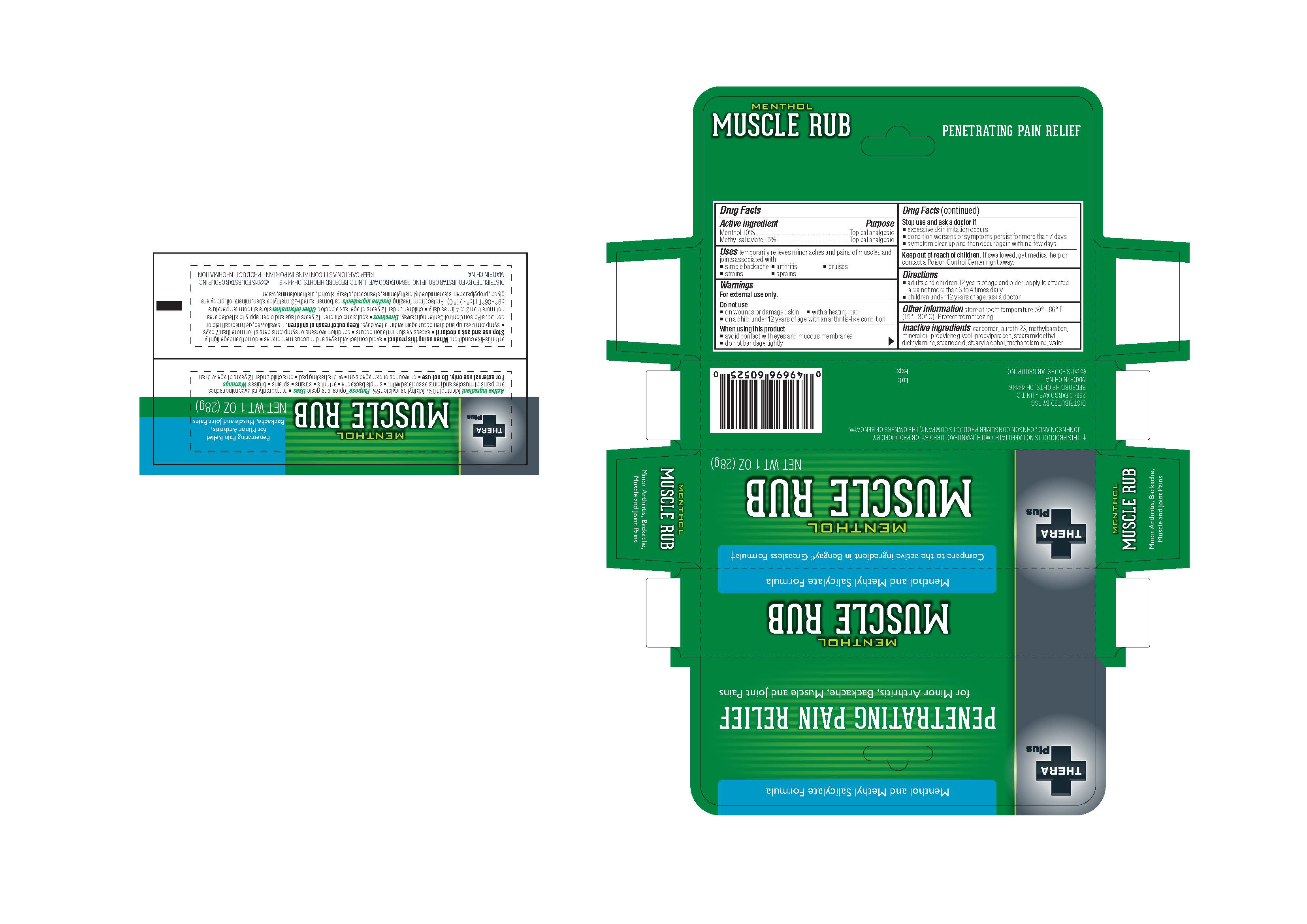 DRUG LABEL: 
                  TheraPlus
				

                
                  

NDC: 55621-004 | Form: OINTMENT
Manufacturer: Zhejiang Jingwei Pharmaceutical Co., Ltd.
Category: otc | Type: HUMAN OTC DRUG LABEL
Date: 20231024

ACTIVE INGREDIENTS: MENTHOL 10 g/100 g; MENTHYL SALICYLATE, (+/-)- 15 g/100 g
INACTIVE INGREDIENTS: LAURETH-23; METHYLPARABEN; MINERAL OIL; PROPYLENE GLYCOL; PROPYLPARABEN; STEARIC ACID; STEARYL ALCOHOL; TROLAMINE; WATER

Drug Facts

INACTIVE INGREDIENT

carbomer, laureth-23, methylparaben, mineral oil, propylene glycol, propylparaben, stearamidoethyl diethylamine, stearic acid, stearyl alcohol, triethanomoline, water Inactive Ingredients

Active Ingredient

Menthol 10%

Menthol salicylate 15%

Warnings

For external use only.

Do not use

-on wounds or damaged skin -with a heating pad - on a child under 12 years of age with arthritis-like condition

When using this product

-avoid contact with eyes and mucous membranes -do not bandage tightly

Purpose

Topical analgesic

KEEP OUT OF REACH OF CHILDREN

. If swallowed, get medical help or contact a Poison Control Center right away Keep out of reach of children

INDICATIONS AND USAGE

temporarily relieves minor aches and pains of muscles and joints associated with: Uses

-simple backache -arthritis -bruises -strains -sprains

Directions

-adults and children 12 years of age and older: apply to all affected area not more than 3 to 4 times daily

-children under 12 years of age: ask a doctor